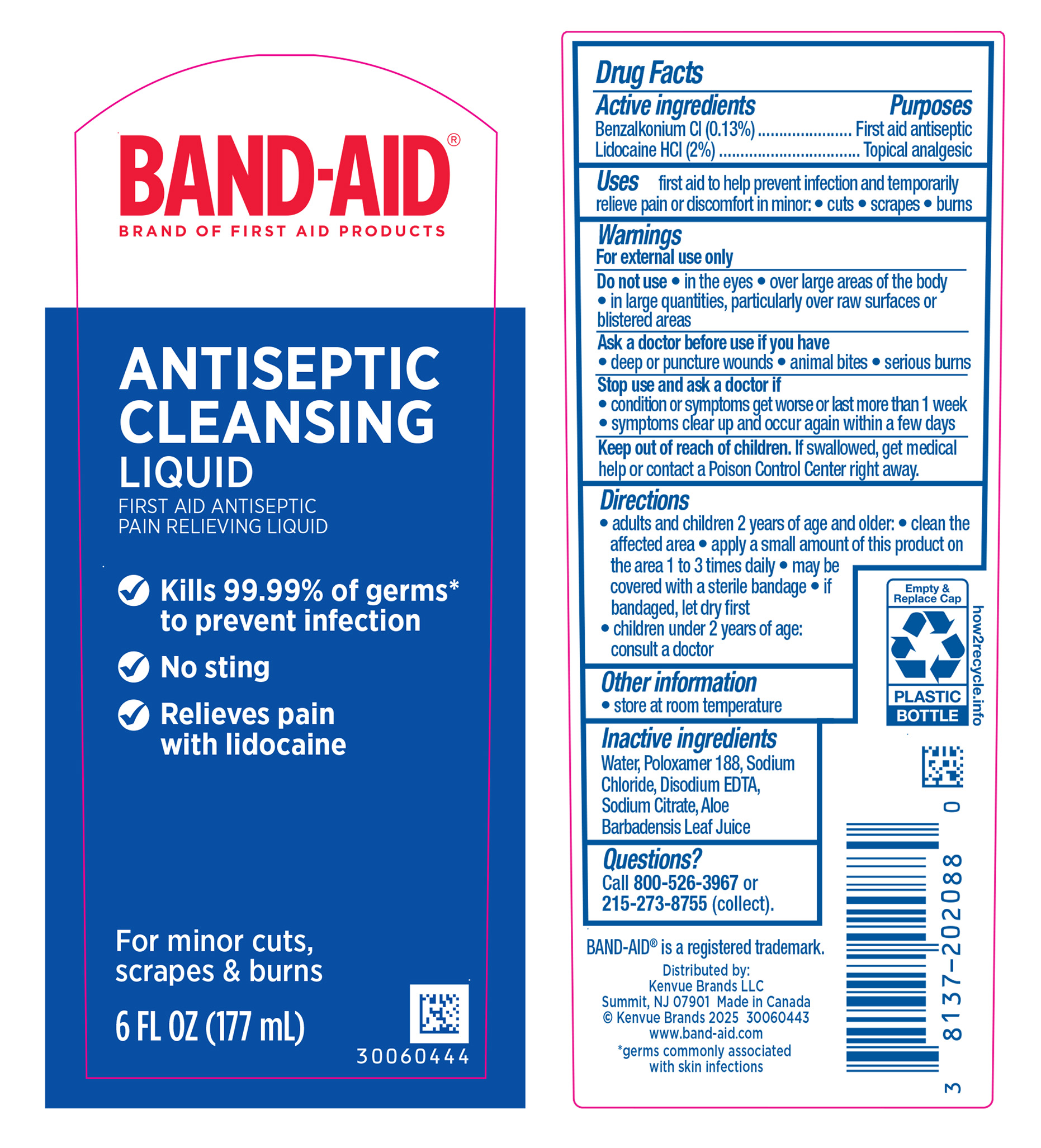 DRUG LABEL: Band Aid Antiseptic Cleansing Liquid
NDC: 69968-0730 | Form: LIQUID
Manufacturer: Kenvue Brands LLC
Category: otc | Type: HUMAN OTC DRUG LABEL
Date: 20250526

ACTIVE INGREDIENTS: BENZALKONIUM CHLORIDE 1.3 mg/1 mL; LIDOCAINE HYDROCHLORIDE 20 mg/1 mL
INACTIVE INGREDIENTS: ALOE VERA LEAF; EDETATE DISODIUM; POLOXAMER 188; SODIUM CHLORIDE; SODIUM CITRATE, UNSPECIFIED FORM; WATER

Band Aid Antiseptic Cleansing Liquid

Drug Facts

ACTIVE INGREDIENT

Benzalkonium Cl (0.13%)
Lidocaine HCl (2%)

PURPOSE

Benzalkonium Cl -
First aid antiseptic

Lidocaine HCl - Topical analgesic

Uses

first aid to help prevent infection and temporarily relieve pain or discomfort in minor:

- cuts
- scrapes
- burns

Warnings

For external use only

Do not use

- in the eyes
- over large areas of the body
- in large quantities, particularly over raw surfaces or blistered areas.

Ask a doctor before use if you have

- deep or puncture wounds
- animal bites
- serious burns

Stop use and ask a doctor if

- condition or symptoms get worse or last more than 1 week
- symptoms clear up and occur again within a few days

Keep out of reach of children. If swallowed, get medical help or contact a Poison Control Center right away.

Directions

- adults and children 2 years of age and older:
  - clean the affected area
  - apply a small amount of this product on the area 1 to 3 times daily
  - may be covered with a sterile bandage
  - if bandaged, let dry first
- children under 2 years of age: consult a doctor

Other information

- store at room temperature

Inactive ingredients

Water, Poloxamer 188, Sodium Chloride, Disodium EDTA, Sodium Citrate, Aloe Barbadensis Leaf Juice

Questions?

Call 800-526-3967 or 215-273-8755 (collect).

Distributed by:

Kenvue Brands LLC
Summit, NJ 07901

PRINCIPAL DISPLAY PANEL - 177 mL Bottle Label

BAND-AID®
BRAND OF FIRST AID PRODUCTS
ANTISEPTIC

CLEANSING

LIQUID
FIST AID ANTISEPTIC

PAIN RELIEVING LIQUID

Kills 99.99% of germs*

to prevent infection

No sting

Relieves pain

with lidocaine

For minor cuts,
scrapes & burns
6 FL OZ (177 mL)